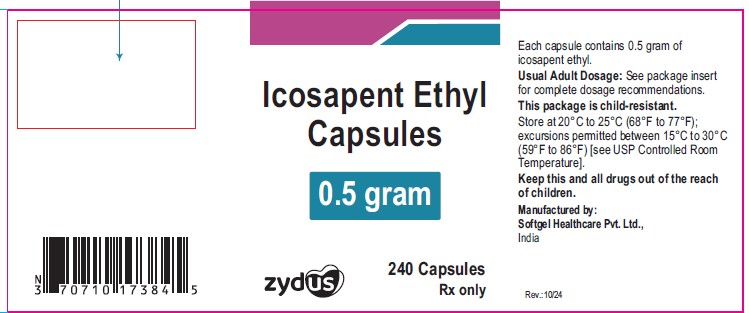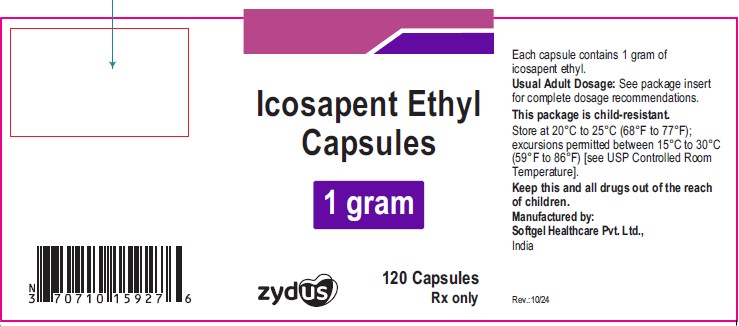 DRUG LABEL: icosapent ethyl
NDC: 35916-1738 | Form: CAPSULE
Manufacturer: Softgel Healthcare Private Limited
Category: prescription | Type: HUMAN PRESCRIPTION DRUG LABEL
Date: 20241025

ACTIVE INGREDIENTS: ICOSAPENT ETHYL 0.5 g/1 1
INACTIVE INGREDIENTS: .ALPHA.-TOCOPHEROL; GELATIN; GLYCERIN; WATER; TITANIUM DIOXIDE; SHELLAC

ICOSAPENT ETHYL capsules, for oral use

PACKAGE LABEL.PRINCIPAL DISPLAY PANEL

NDC 35916-1738-1

Icosapent Ethyl Capsules

0.5 gram

240 capsules

Rx only

NDC 35916-1592-1

Icosapent Ethyl Capsules

1 gram

240 capsules

Rx only